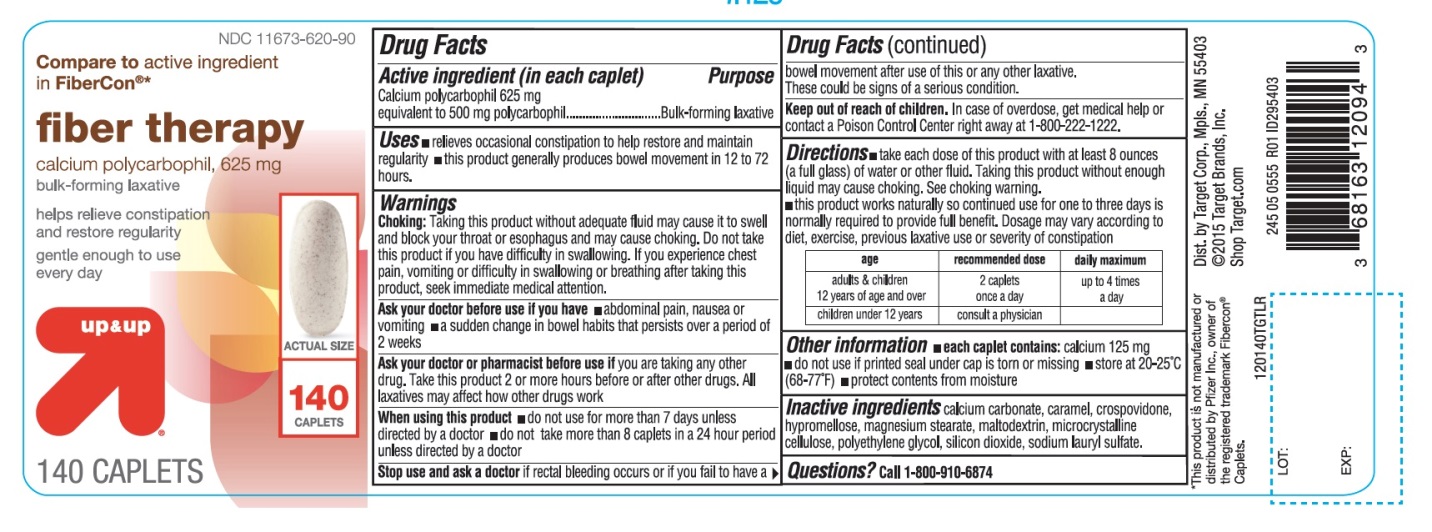 DRUG LABEL: up and up fiber therapy
NDC: 11673-620 | Form: TABLET
Manufacturer: Target Corporation.
Category: otc | Type: HUMAN OTC DRUG LABEL
Date: 20251104

ACTIVE INGREDIENTS: CALCIUM POLYCARBOPHIL 625 mg/1 1
INACTIVE INGREDIENTS: CALCIUM CARBONATE; CARAMEL; CROSPOVIDONE (120 .MU.M); HYPROMELLOSE 2208 (100 MPA.S); MAGNESIUM STEARATE; MALTODEXTRIN; MICROCRYSTALLINE CELLULOSE; POLYETHYLENE GLYCOL 800; SILICON DIOXIDE; SODIUM LAURYL SULFATE

up and up fiber therapy

Active ingredient (in each caplet)

Calcium polycarbophil 625 mg equivalent to 500 mg polycarbophil

Purpose

Bulk-forming laxative

Uses

- relieves occasional constipation to help restore and maintain regularity
- this product generally produces bowel movement in 12 to 72 hours.

Warnings

Choking:Taking this product without adequate fluid may cause it to swell and block your throat or esophagus and may cause choking. Do not take this product if you have difficulty in swallowing. If you experience chest pain, vomiting or difficulty in swallowing or breathing after taking this product, seek immediate medical attention.

Ask your doctor before use if you have

- abdominal pain, nausea or vomiting
- a sudden change in bowel habits that persists over a period of 2 weeks

Ask your doctor or pharmacist before use if

you are taking any other drug. Take this product 2 or more hours before or after other drugs. All laxatives may affect how other drugs work.

When using this product

- do not use for more than 7 days unless directed by a doctor
- do not take more than 8 caplets in a 24 hour period unless directed by a doctor

Stop use and ask a doctor

if rectal bleeding occurs or if you fail to have a bowel movement after use of this or any other laxative. These could be signs of a serious condition.

Keep out of reach of children.

In case of overdose, get medical help or contact a Poison Control Center right away at 1-800-222-1222.

Directions

- take each dose of this product with at least 8 ounces (a full glass) of water or other fluid. Taking this product without enough liquid may cause choking. See choking warning.
- this product works naturally so continued use for one to three days is normally required to provide full benefit. Dosage may vary according to diet, exercise, previous laxative use or severity of constipation

1. age

1. recommended dose

1. daily maximum

1. adults & children 12 years of age and over

1. 2 caplets once a day

1. up to 4 times a day

1. children under 12 years

1. consult a physician

Other information

- each caplet contains: calcium 125 mg
- do not use if printed seal under cap is torn or missing
- store at 20-25°C (68-77°F)
- protect contents from moisture

Inactive ingredients

calcium carbonate, caramel, crospovidone, hypromellose, magnesium stearate, maltodextrin, microcrystalline cellulose, polyethylene glycol, silicon dioxide, sodium lauryl sulfate

Questions?

Call 1-800-910-6874

Principal Display Panel

NDC 11673-620-90

Compare toactive ingredient in Fibercon® *

fiber therapy

calcium polycarbophil ,625 mg

bulk-forming laxative

helps relieve constipation and restore regularity

gentle enough to use every day

140 CAPLETS

*This product is not manufactured or distributed by Pfizer Inc., owner of the registered trademark Fibercon® Caplets.

245 05 0555 R01 ID295403

Dist.by Target Corp., Mpls., MN 55403

©2015 Target Brands, Inc.

Shop Target.com